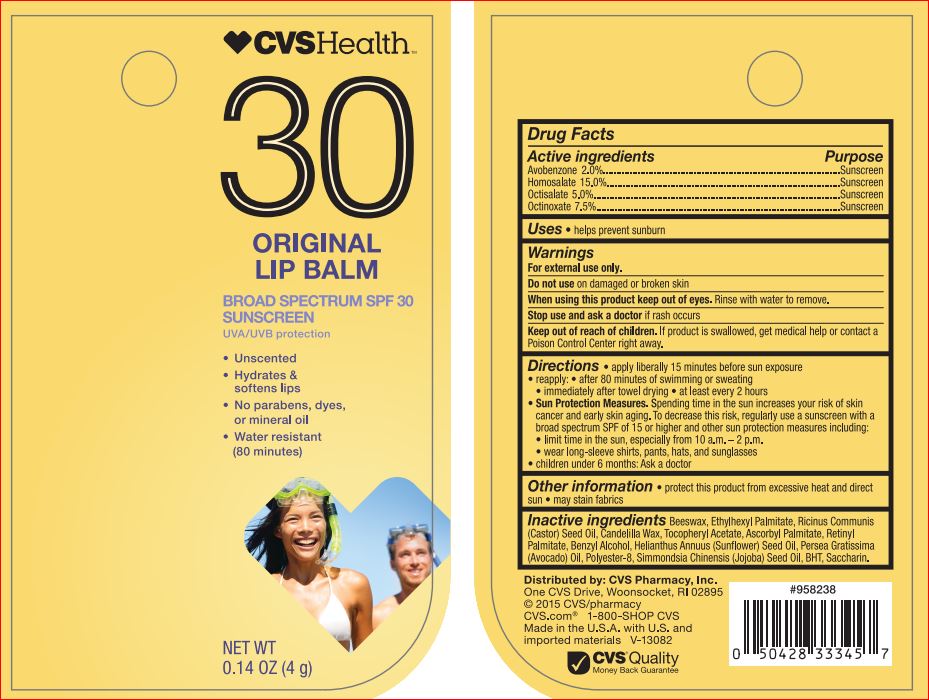 DRUG LABEL: LIP BALM MINT
NDC: 69842-033 | Form: STICK
Manufacturer: CVS
Category: otc | Type: HUMAN OTC DRUG LABEL
Date: 20171205

ACTIVE INGREDIENTS: Avobenzone 2 g/100 g; Homosalate 15 g/100 g; Octisalate 5 1/100 g; Octinoxate 7.5 g/100 g
INACTIVE INGREDIENTS: Ascorbyl Palmitate; YELLOW WAX; Benzyl Alcohol; BUTYLATED HYDROXYTOLUENE; Candelilla Wax; Ethylhexyl Palmitate; SUNFLOWER OIL; AVOCADO OIL; POLYESTER-8 (1400 MW, CYANODIPHENYLPROPENOYL CAPPED); VITAMIN A PALMITATE; CASTOR OIL; Saccharin; JOJOBA OIL; .ALPHA.-TOCOPHEROL ACETATE

Drug Facts

Active ingredients Purpose

Avobenzone - 2.00% Sunscreen
Homosalate - 15.00% Sunscreen
Octisalate - 5.00% Sunscreen
Octinoxate – 7.50% Sunscreen

INDICATIONS AND USAGE

Uses helps prevent sunburn

Warnings For external use only

Do not use on damage or broken skin

When using this product keep out of eyes. Rinse with water to remove.

Stop use and ask a doctor if rash occurs

Keep out of reach of the children
If product is swallowed, get medical help or contact a Poison Control Center right away

Directions

• apply liberally 15 minutes before sun exposure
• reapply:
- after 80 minutes of swimming or sweating
- immediately after towel drying
- at least every 2 hours
• Sun Protection Measures. Spending time in the sun increases your risk of skin cancer and early skin aging. To decrease this risk, regularly use a sunscreen SPF of 15 or higher and other sun protection measures including:
- limit time in the sun, especially from 10 a.m. – 2 p.m.
- wear long sleeve shirts, pants, hats, and sunglasses
• children under 6 month: Ask a doctor

Inactive ingredients

Ascorbyl Palmitate, Beeswax, Benzyl Alcohol, BHT, Candelilla Wax, Ethylhexyl Palmitate, Helianthus Annuus (Sunflower) Seed Oil, Persea , Gratissima (Avocado) Oil, Polyester-8, Retinyl Palmitate, Ricinus Communis (Castor) Seed Oil, Saccharin, Simmondsia Chinensis (Jojoba) , Seed Oil, Tocopheryl Acetate